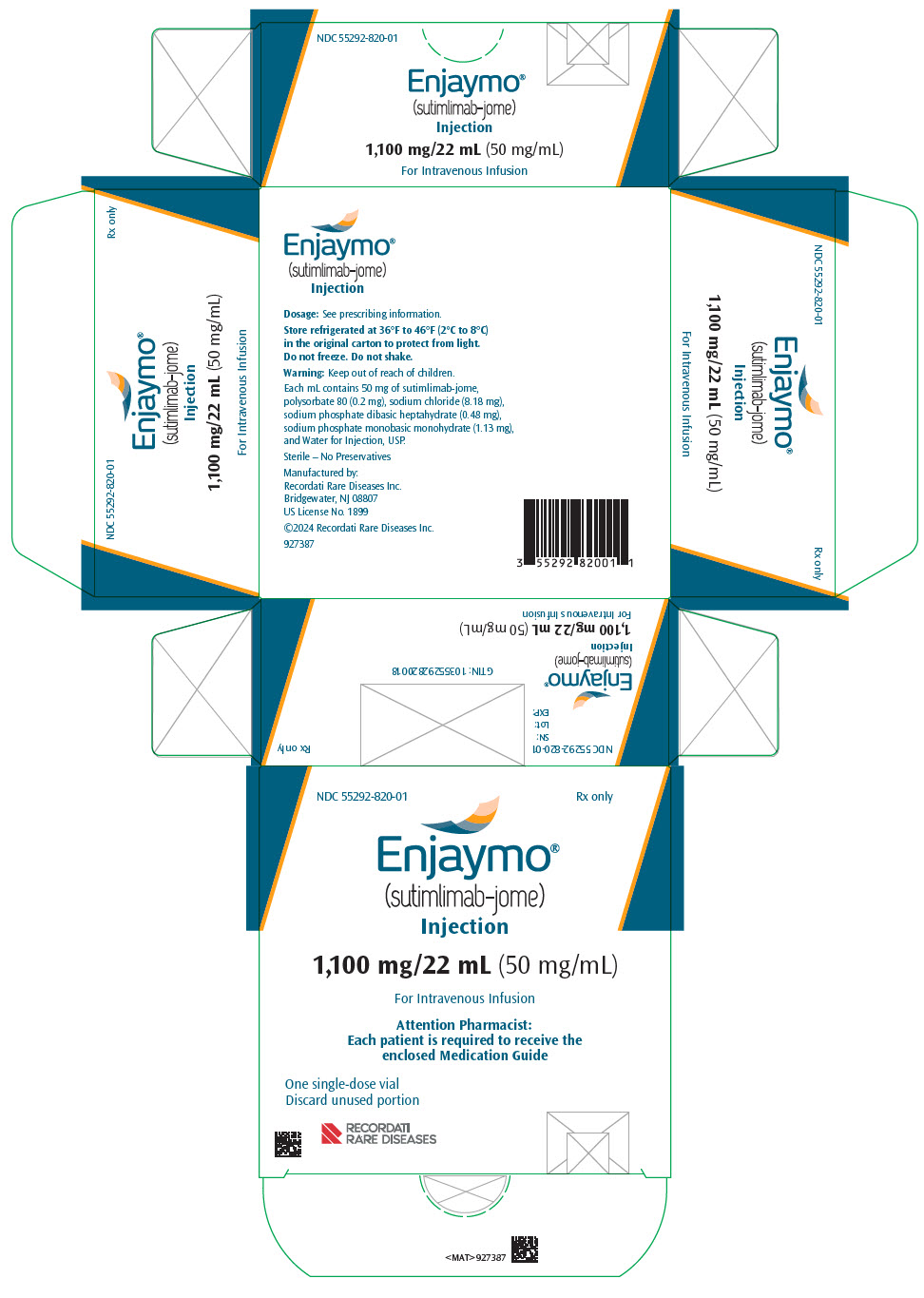 DRUG LABEL: Enjaymo
NDC: 55292-820 | Form: INJECTION, SOLUTION, CONCENTRATE
Manufacturer: Recordati Rare Diseases, Inc.
Category: prescription | Type: HUMAN PRESCRIPTION DRUG LABEL
Date: 20250625

ACTIVE INGREDIENTS: SUTIMLIMAB 50 mg/1 mL
INACTIVE INGREDIENTS: POLYSORBATE 80 0.2 mg/1 mL; SODIUM CHLORIDE 8.18 mg/1 mL; SODIUM PHOSPHATE, DIBASIC, HEPTAHYDRATE 0.48 mg/1 mL; SODIUM PHOSPHATE, MONOBASIC, MONOHYDRATE 1.13 mg/1 mL; WATER

HIGHLIGHTS OF PRESCRIBING INFORMATION

These highlights do not include all the information needed to use ENJAYMO safely and effectively. See full prescribing information for ENJAYMO.
ENJAYMO® (sutimlimab-jome) injection, for intravenous use
Initial U.S. Approval: 2022

RECENT MAJOR CHANGES

Dosage and Administration (2.1) | 02/2024
Warnings and Precautions (5.1) | 02/2024

1 INDICATIONS AND USAGE

ENJAYMO is a classical complement inhibitor indicated for the treatment of hemolysis in adults with cold agglutinin disease (CAD). (1)

2 DOSAGE AND ADMINISTRATION

- Vaccinate against encapsulated bacteria at least two weeks prior to treatment. (2.1)
- Weight-based dosage weekly for two weeks then every two weeks:
  - For patients weighing 39 kg to less than 75 kg: 6,500 mg by intravenous infusion. (2.2)
  - For patients weighing 75 kg or more: 7,500 mg by intravenous infusion. (2.2)
- See Full Prescribing Information for important preparation and administration instructions. (2.2, 2.3)

3 DOSAGE FORMS AND STRENGTHS

Injection: 1,100 mg/22 mL (50 mg/mL) in a single-dose vial (3)

4 CONTRAINDICATIONS

ENJAYMO is contraindicated in patients with known hypersensitivity to sutimlimab-jome or any of the inactive ingredients. (4)

5 WARNINGS AND PRECAUTIONS

- Serious Infections: Ensure patients are vaccinated against encapsulated bacteria. Monitor patients for early signs and symptoms of infections. (5.1)
- Infusion-Related Reactions: Monitor patients for infusion-related reactions, interrupt if reaction occurs, and institute appropriate medical management as needed. (5.2)
- Risk of Autoimmune Disease: Monitor patients for signs and symptoms and manage medically. (5.3)
- Recurrent Hemolysis After ENJAYMO Discontinuation: Monitor patients for signs and symptoms of hemolysis if treatment with ENJAYMO is interrupted. (5.4)

6 ADVERSE REACTIONS

Most common adverse reactions in the CADENZA study (Part A) (incidence ≥18%) are rhinitis, headache, hypertension, acrocyanosis, and Raynaud's phenomenon. The most common adverse reactions in the CARDINAL study (incidence ≥25%) are urinary tract infection, respiratory tract infection, bacterial infection, dizziness, fatigue, peripheral edema, arthralgia, cough, hypertension, and nausea. (6.1)

To report SUSPECTED ADVERSE REACTIONS, contact Recordati Rare Diseases Inc. at 1-888-575-8344 or FDA at 1-800-FDA-1088 or www.fda.gov/medwatch.

FULL PRESCRIBING INFORMATION

1 INDICATIONS AND USAGE

Cold Agglutinin Disease

ENJAYMO (sutimlimab-jome) is indicated for the treatment of hemolysis in adults with cold agglutinin disease (CAD).

2 DOSAGE AND ADMINISTRATION

2.1 Recommended Vaccinations for Encapsulated Bacterial Infections

Vaccinate patients against encapsulated bacteria, including Streptococcus pneumoniae and Neisseria meningitidis (serogroups A, C, W, Y and B), according to current Advisory Committee on Immunization Practices (ACIP) recommendations at least 2 weeks prior to initiation of ENJAYMO [see Warnings and Precautions (5.1)]. If urgent ENJAYMO therapy is indicated in a patient who is not up to date with vaccines for Streptococcus pneumoniae and Neisseria meningitidis administer these vaccines as soon as possible.

2.2 Recommended Dosage Regimen

The recommended dosage of ENJAYMO for patients with CAD is based on body weight. For patients weighing 39 kg to less than 75 kg, the recommended dose is 6,500 mg and for patients weighing 75 kg or more, the recommended dose is 7,500 mg. Administer ENJAYMO intravenously weekly for the first two weeks, with administration every two weeks thereafter. Administer ENJAYMO at the recommended dosage regimen time points, or within two days of these time points.

If a dose is missed, administer as soon as possible; thereafter, resume dosing every two weeks. If the duration after the last dose exceeds 17 days, administer ENJAYMO weekly for two weeks, with administration every two weeks thereafter.

2.3 Preparation and Administration

ENJAYMO is for intravenous infusion only.

Each vial of ENJAYMO is intended for single dose only.

ENJAYMO can either be used as an undiluted or diluted preparation.

Undiluted preparation of ENJAYMO

Use aseptic technique to prepare ENJAYMO as follows:

- Remove ENJAYMO from the refrigerator. To minimize foaming, do not shake ENJAYMO.
- Inspect vials visually for particulate matter and discoloration prior to administration. ENJAYMO solution is a clear to slightly opalescent and colorless to slightly yellow liquid. Do not administer if discolored or if other foreign particulate matter is present.
- Withdraw the calculated volume of ENJAYMO from the appropriate number of vials based on the recommended dosage (see Table 1) and add to an empty infusion bag.
- Prior to administration, allow the infusion solution to adjust to room temperature (59°F to 77°F (15°C to 25°C). Refer to Table 1 for infusion rate. The infusion should be administered over 1 hour. Administer ENJAYMO infusion solution only through a 0.2 micron in-line filter with a polyethersulfone (PES) membrane.
- The infusion catheter and tubing should be primed with the dosing solution immediately before infusion and flushed immediately following completion of the infusion with a sufficient quantity (approximately 20 mL) of sterile 0.9% Sodium Chloride Injection, USP.
- If the ENJAYMO infusion solution is not used immediately, store refrigerated at 36°F to 46°F (2°C to 8°C).
- Once removed from refrigeration, allow the ENJAYMO infusion solution to adjust to room temperature 59°F to 77°F (15°C to 25°C) and administer within 8 hours. Total time from the time of preparation, including refrigeration, adjustment to room temperature and the expected infusion time should not exceed 36 hours. In-line infusion warmers may be used, do not exceed a temperature of 104°F (40°C).
- No incompatibilities have been observed between ENJAYMO infusion solution and infusion bags made of Di-(2-ethylhexyl)phthalate (DEHP) plasticized polyvinyl chloride (PVC), Ethyl Vinyl Acetate (EVA) and polyolefin (PO); administration sets made of DEHP-plasticized PVC, DEHP-free polypropylene (PP) and polyethylene (PE); and vial adapters made of polycarbonate (PC) and acrylonitrile-butadiene-styrene (ABS).

Table 1: Infusion Reference Table for ENJAYMO (undiluted)
Body Weight Range | Dose | Number of ENJAYMO Vials Needed | ENJAYMO Volume | Maximum Infusion Rate
Greater than or equal to 39 kg to less than 75 kg | 6,500 mg | 6 | 130 mL | 130 mL/hour [Patients with cardiopulmonary disease may receive the infusion over 120 minutes.]
75 kg or greater | 7,500 mg | 7 | 150 mL | 150 mL/hour

Diluted preparation of ENJAYMO

Use aseptic technique to prepare ENJAYMO as follows:

- Remove ENJAYMO from the refrigerator. To minimize foaming, do not shake ENJAYMO.
- Parenteral drug products should be inspected visually for particulate matter and discoloration prior to administration, whenever solution and container permit.
- ENJAYMO solution is a clear to slightly opalescent and colorless to slightly yellow solution. Do not administer if discolored or if foreign particulate matter is present.
- Withdraw the calculated volume of ENJAYMO from the appropriate number of vials based on the recommended dosage (see Table 1). Dilute the calculated volume with 0.9% Sodium Chloride Injection, USP to a total volume of 500 mL.
- Refer to Table 2 for infusion rate. Administer the infusion over 1 to 2 hours depending on the patient's body weight. Administer ENJAYMO infusion solution only through a 0.2 micron in-line filter with a polyethersulfone (PES) membrane.
- Prime the infusion tubing with the dosing solution immediately before infusion and flush immediately following completion of the infusion with a sufficient quantity (approximately 20 mL) of 0.9% Sodium Chloride Injection, USP.
- If the ENJAYMO infusion solution is not used immediately, store refrigerated at 36°F to 46°F (2°C to 8°C).
- Once removed from refrigeration, allow the ENJAYMO infusion solution to adjust to room temperature 59°F to 77°F (15°C to 25°C) and administer within 8 hours. Total time from the time of preparation, including refrigeration, adjustment to room temperature and the expected infusion time should not exceed 36 hours. In-line infusion warmers may be used; do not exceed a temperature of 104°F (40°C).
- No incompatibilities have been observed between ENJAYMO infusion solution and infusion bags made of Di-(2-ethylhexyl)phthalate (DEHP) plasticized polyvinyl chloride (PVC), Ethyl Vinyl Acetate (EVA) and polyolefin (PO); administration sets made of DEHP-plasticized PVC, DEHP-free polypropylene (PP) and polyethylene (PE); and vial adapters made of polycarbonate (PC) and acrylonitrile-butadiene-styrene (ABS).

Table 2: Infusion Reference Table for ENJAYMO (diluted in 0.9% Sodium Chloride Injection, USP)
Body Weight Range | Dose | Number of ENJAYMO Vials Needed | ENJAYMO Volume | Volume of NaCl Diluent | Total Volume | Maximum Infusion Rate
39 kg to less than 70 kg | 6,500 mg | 6 | 130 mL | 370 mL | 500 mL | 250 mL/hour
70 kg to less than 75 kg | 6,500 mg | 6 | 130 mL | 370 mL | 500 mL | 500 mL/hour [Patients with cardiopulmonary disease may receive the infusion over 120 minutes.]
75 kg or greater | 7,500 mg | 7 | 150 mL | 350 mL | 500 mL | 500 mL/hour

Slow or stop the infusion in case of infusion reaction during ENJAYMO administration. Monitor the patient for at least two hours following completion of the initial infusion for signs or symptoms of an infusion and/or hypersensitivity reaction. Monitor the patient for one hour following completion of subsequent infusions for signs or symptoms of an infusion reaction.

3 DOSAGE FORMS AND STRENGTHS

Injection: 1,100 mg/22 mL (50 mg/mL) as a clear to slightly opalescent, colorless to slightly yellow solution in a single-dose vial.

4 CONTRAINDICATIONS

ENJAYMO is contraindicated in patients with known hypersensitivity to sutimlimab-jome or any of the inactive ingredients [see Warnings and Precautions (5.2) and Adverse Reactions (6.1)].

5 WARNINGS AND PRECAUTIONS

5.1 Serious Infections Including Those Caused by Encapsulated Bacteria

ENJAYMO, a proximal classical complement C1s inhibitor, increases a patient's susceptibility to serious infections including those caused by encapsulated bacteria e.g. Neisseria meningitidis (any serogroup, including non-groupable strains), Streptococcus pneumoniae, and Haemophilus influenzae type B.

Life-threatening and fatal infections with encapsulated bacteria have occurred in both vaccinated and unvaccinated patients treated with complement inhibitors.

Serious infections (bacterial and viral) were reported in 15% (10/66) of patients receiving ENJAYMO from the two phase 3 studies. These infections included urinary tract infection with sepsis, respiratory tract infection, pneumonia, otomastoiditis, and skin infections One patient (1.5%) died due to klebsiella pneumonia.

Complete or update vaccination against encapsulated bacteria at least 2 weeks prior to administration of the first dose of ENJAYMO, according to the most current ACIP recommendations for patients receiving a complement inhibitor. Revaccinate patients in accordance with ACIP recommendations considering the chronic duration of therapy with ENJAYMO. Note that, ACIP recommends an administration schedule in patients receiving complement inhibitors that differs from the administration schedule in the vaccine prescribing information. If urgent ENJAYMO therapy is indicated in a patient who is not up to date on their vaccines administer vaccine(s) as soon as possible.

Vaccination does not eliminate the risk of serious encapsulated bacterial infections, despite development of antibodies following vaccination. Closely monitor patients for early signs and symptoms of serious infection and evaluate patients immediately if an infection is suspected.

If ENJAYMO treatment is administered to patients with active systemic infections, monitor closely for signs and symptoms of worsening infection. Some infections may become rapidly life-threatening or fatal if not recognized and treated promptly. Inform patients of these signs and symptoms and steps to be taken to seek immediate medical care. Consider interruption of ENJAYMO treatment in patients who are undergoing treatment for serious infection. ENJAYMO has not been studied in patients with chronic systemic infections such as hepatitis B, hepatitis C, or HIV. Consider patients' immune status when initiating treatment with ENJAYMO.

5.2 Infusion-Related Reactions

ENJAYMO is contraindicated in patients with known hypersensitivity to sutimlimab-jome or any of the inactive ingredients [see Contraindications (4)]. Administration of ENJAYMO may result in infusion-related reactions. In the two phase 3 studies, 19 of 66 (29%) patients treated with ENJAYMO experienced infusion-related reactions (e.g., shortness of breath, rapid heartbeat, nausea, flushing, headache, hypotension, chest discomfort, pruritus, rash, injection site reaction, and dizziness) were reported in patients from the two clinical studies. One patient permanently discontinued ENJAYMO due to an infusion-related reaction.

Monitor patients for infusion-related reactions and interrupt if a reaction occurs. Discontinue ENJAYMO infusion and institute appropriate supportive measures if signs of hypersensitivity reactions, such as cardiovascular instability or respiratory compromise, occur.

5.3 Risk of Autoimmune Disease

Based on its mechanism of action, ENJAYMO may potentially increase the risk for developing autoimmune diseases such as systemic lupus erythematosus (SLE). Development of systemic lupus erythematosus (SLE) has been associated with inherited classical complement deficiency. Patients with SLE or autoimmune disease with positive anti-nuclear antibody were excluded from clinical trials with ENJAYMO. In clinical trials, 3/66 (4.5%) patients developed a relapse or worsening of preexisting autoimmune disease. Monitor patients being treated with ENJAYMO for signs and symptoms and manage medically.

5.4 Recurrent Hemolysis After ENJAYMO Discontinuation

If treatment with ENJAYMO is interrupted, closely monitor patients for signs and symptoms of recurrent hemolysis, e.g., elevated levels of total bilirubin or lactate dehydrogenase (LDH) accompanied by a decrease in hemoglobin, or reappearance of symptoms such as fatigue, dyspnea, palpitations, or hemoglobinuria. Consider restarting ENJAYMO if signs and symptoms of hemolysis occur after discontinuation.

6 ADVERSE REACTIONS

The following clinically significant adverse reactions are discussed in greater detail in other sections of the labeling:

- Serious Infections [see Warnings and Precautions (5.1)]
- Infusion-Related Reactions [see Warnings and Precautions (5.2)]
- Risk of Autoimmune Disease [see Warnings and Precautions (5.3)]
- Recurrent Hemolysis After ENJAYMO Discontinuation [see Warnings and Precautions (5.4)]

6.1 Clinical Trials Experience

Because clinical trials are conducted under widely varying conditions, adverse reaction rates observed in the clinical trials of a drug cannot be directly compared to rates in the clinical trials of another drug and may not reflect the rates observed in practice.

The safety of ENJAYMO in patients with a confirmed diagnosis of CAD was evaluated in a placebo-controlled study (CADENZA) in Part A (n=42) followed by an open-label single-arm study in Part B (n=39) and an open-label single-arm study (CARDINAL) (n=24) [see Clinical Studies (14)]. The median duration of treatment exposure to ENJAYMO was 104 weeks (patients randomized to ENJAYMO in CADENZA Part A) and 93 weeks (patients randomized to placebo in CADENZA Part A) and 143 weeks for CARDINAL.

CADENZA (Part A)

Serious adverse reaction occurred in 2/22 (9%) patients who received ENJAYMO. Serious adverse reactions included Raynaud's phenomenon (n=1) and febrile infection (n=1).

Permanent discontinuation of ENJAYMO due to an adverse reaction occurred in 2/22 (9%) patients. Adverse reactions which resulted in permanent discontinuation of ENJAYMO included Raynaud's phenomenon (n=1), acrocyanosis (n=1), and infusion related reactions (n=1).

Dosage interruptions of ENJAYMO due to an adverse reaction occurred in 3/22 patients. Adverse reactions which required dosage interruption included nasopharyngitis (n=1) and infusion related reaction (n=1), including pruritis (n=1) and chest discomfort (n=1).

The most common adverse reactions (≥18%) reported in the CADENZA study were rhinitis, headache, hypertension, acrocyanosis, and Raynaud's phenomenon.

Table 3: Adverse Reactions (≥10%) in Patients Who Received ENJAYMO with a Difference Between Arms of >5% Compared to Placebo in the CADENZA Study (Part A)
Adverse Reactions | ENJAYMO (N=22) | Placebo (N=20)
Headache | 5 (23%) | 2 (10%)
Hypertension | 5 (23%) | 0
Rhinitis | 4 (18%) | 0
Acrocyanosis | 4 (18%) | 0
Raynaud's phenomenon | 4 (18%) | 0

CARDINAL

Serious adverse reactions occurred in 10/24 (42%) patients who received ENJAYMO. The most common adverse reaction (>5%) was acrocyanosis (n=2). A fatal adverse reaction of pneumonia klebsiella occurred in one patient who received ENJAYMO.

Permanent discontinuation of ENJAYMO due to an adverse reaction occurred in 2/24 (8%) patients. Adverse reactions which resulted in permanent discontinuation of ENJAYMO included pneumonia klebsiella (n=1) and acrocyanosis (n=2).

Dosage interruptions of ENJAYMO due to an adverse reaction occurred in 7/24 patients. Adverse reactions which required dosage interruption included pneumonia, COVID-19 pneumonia, abdominal pain upper, urinary tract infection bacterial, urosepsis, acrocyanosis, viral infection, blood creatinine increased and infusion-related reaction.

The most common adverse reaction (≥25%) reported in the CARDINAL study were urinary tract infection, respiratory tract infection, bacterial infection, dizziness, fatigue, peripheral edema, arthralgia, cough, hypertension, and nausea.

Table 4: Adverse Reactions (≥15%) in Patients Receiving ENJAYMO in the CARDINAL Study
Adverse Reaction/Body System | n (%) (N=24)
INFECTIONS AND INFESTATIONS
Urinary tract infection [Urinary Tract Infection includes cystitis, urosepsis] | 9 (38%)
Respiratory tract infection [Respiratory tract infection includes upper respiratory tract infection, bronchitis, lower respiratory tract infection, COVID-19 pneumonia] | 6 (25%)
Bacterial infection [Bacterial infection includes Escherichia urinary tract infection, urinary tract infection bacteria, cystitis bacterial, Escherichia sepsis, pneumococcal sepsis, pneumonia klebsiella, streptococcal sepsis, wound infection staphylococcal] | 6 (25%)
Nasopharyngitis | 5 (21%)
Viral infection [Viral infection includes oral herpes, herpes zoster, respiratory tract infection viral, viral upper respiratory tract infection, Herpes simplex viraemia] | 5 (21%)
NERVOUS SYSTEM DISORDERS
Dizziness [Dizziness includes dizziness postural and vertigo] | 7 (29%)
Headache | 5 (21%)
GENERAL DISORDERS
Fatigue [Fatigue includes asthenia, malaise, mental fatigue] | 8 (33%)
Peripheral edema [Peripheral edema includes peripheral swelling] | 6 (25%)
Pyrexia | 5 (21%)
MUSCULOSKELETAL AND CONNECTIVE TISSUE DISORDERS
Arthralgia | 6 (25%)
VASCULAR DISORDERS
Hypertension [Hypertension includes, blood pressure increased, essential hypertension] | 6 (25%)
Acrocyanosis | 5 (21%)
GASTROINTESTINAL DISORDERS
Nausea | 6 (25%)
Abdominal pain [Abdominal pain includes abdominal pain upper, abdominal tenderness] | 5 (21%)
RESPIRATORY, THORACIC, AND MEDIASTINAL DISORDERS
Cough [Cough includes productive cough] | 6 (25%)
INJURY, POISONING AND PROCEDURAL COMPLICATIONS
Infusion-related reaction [Infusion related reaction includes stress cardiomyopathy, feeling cold (All occurred within 24 hours of start of ENJAYMO infusion)] | 4 (17%)
Please note: if a subject has multiple events in a grouped term the subject is only counted once.
The following terms were combined for the analysis:

8 USE IN SPECIFIC POPULATIONS

8.1 Pregnancy

Risk Summary

There are no available data on ENJAYMO use in pregnant women to evaluate for a drug-associated risk of major birth defects, miscarriage, or adverse maternal or fetal outcomes. Human immunoglobulin G (IgG) antibodies are known to cross the placental barrier; therefore, sutimlimab-jome may be transmitted from the mother to the developing fetus. In animal reproduction studies, intravenous administration of sutimlimab-jome to pregnant monkeys during organogenesis at doses 2 to 3 times the maximum recommended human doses did not result in adverse effects on pregnancy or offspring development (see Data).

The estimated background risk of major birth defects and miscarriage for the indicated population is unknown. All pregnancies have a background risk of birth defect, loss, or other adverse outcomes. In the U.S. general population, the estimated background risk of major birth defects and miscarriage in clinically recognized pregnancies is 2%-4% and 15%-20%, respectively.

Data

Animal data

Pregnant monkeys were administered sutimlimab-jome at doses of 60 and 180 mg/kg/dose via 30-minute intravenous infusion once-weekly from gestation Day 20 to parturition (approximately 21 doses) resulting in exposures 2 to 3 times the human exposures at the maximum recommended doses, based on area under the curve (AUC). Sutimlimab-jome was detectable in infants born to pregnant females exposed to 180 mg/kg/week. No effects on reproductive and developmental parameters were observed in maternal animals and offspring, respectively.

8.2 Lactation

Risk Summary

There are no data on the presence of sutimlimab-jome in human milk, effects on the breastfed child, or the effects on milk production. Maternal IgG is known to be present in human milk. The effects of local gastrointestinal exposure and limited systemic exposure in the breastfed child to sutimlimab-jome are unknown. No conclusions can be drawn regarding whether or not ENJAYMO is safe for use during breastfeeding. The developmental and health benefits of breastfeeding should be considered along with the mother's clinical need for ENJAYMO and any potential adverse effects on the breastfed child from ENJAYMO or from the underlying maternal condition.

8.4 Pediatric Use

Safety and effectiveness in pediatric patients have not been established.

8.5 Geriatric Use

Of the 66 patients with CAD in clinical studies of ENJAYMO, 65% were 65 years of age and over, including 27% who were 75 years of age and over. No overall differences in safety or effectiveness were observed between these patients and younger patients, and other reported clinical experience has not identified differences in responses between the elderly and younger patients, but greater sensitivity of some older individuals cannot be ruled out.

11 DESCRIPTION

Sutimlimab-jome, a classical complement inhibitor, is a humanized monoclonal antibody expressed by recombinant in Chinese hamster ovary (CHO) cells and produced in vitro using standard mammalian cell culture methods. Sutimlimab-jome is composed of two heterodimers. Each heterodimer is composed of a heavy and a light polypeptide chain. Each heavy chain (H-chain) is composed of 445 amino acids and each light chain (L-chain) contains 216 amino acids. Sutimlimab-jome has a molecular weight of approximately 147 kDa.

ENJAYMO (sutimlimab-jome) injection is a sterile, clear to slightly opalescent, colorless to slightly yellow, preservative-free solution for intravenous use. Each single-dose vial contains 1,100 mg sutimlimab-jome at a concentration of 50 mg/mL with a pH of 6.1. Each mL contains 50 mg of sutimlimab-jome and also contains polysorbate 80 (0.2 mg), sodium chloride (8.18 mg), sodium phosphate dibasic heptahydrate (0.48 mg), sodium phosphate monobasic monohydrate (1.13 mg), and Water for Injection, USP.

12 CLINICAL PHARMACOLOGY

12.1 Mechanism of Action

Sutimlimab-jome is an immunoglobulin G (IgG), subclass 4 (IgG4) monoclonal antibody (mAb) that inhibits the classical complement pathway (CP) and specifically binds to complement protein component 1, s subcomponent (C1s), a serine protease which cleaves C4. Sutimlimab-jome does not inhibit the lectin and alternative pathways. Inhibition of the classical complement pathway at the level of C1s prevents deposition of complement opsonins on the surface of RBCs, resulting in inhibition of hemolysis in patients with CAD.

12.2 Pharmacodynamics

Greater than 90% inhibition of CP was observed following a single sutimlimab-jome infusion and sustained in patients with CAD when sutimlimab-jome concentrations were greater than or equal to 100 mcg/mL. C4 levels returned to normal levels (0.2 g/L) in patients with CAD within one week following the first dose of sutimlimab-jome. Complete CP inhibition following initiation of sutimlimab-jome treatment led to inhibition of hemolysis as evidenced by normalization of bilirubin, decrease in LDH, increase in haptoglobin, and decrease in reticulocytes.

After the first treatment with sutimlimab-jome, near normalization of bilirubin associated with a greater than 1 g/dL increase in hemoglobin was observed, demonstrating the effect of CP inhibition. The extent and duration of the pharmacodynamic response in patients with CAD were exposure dependent for sutimlimab-jome.

12.3 Pharmacokinetics

Following administration of the approved weight-based recommended dosages, the exposure of sutimlimab-jome increases proportionally over a dosage range of 60 mg/kg to 100 mg/kg by intravenous infusion (0.3 to 1.5 times the maximum approved recommended dosage based on 75 kg body weight). Steady state was achieved by Week 7 after starting sutimlimab-jome treatment, with an accumulation ratio of less than 2.

Distribution

Sutimlimab-jome binds to C1s in the serum. The volume of distribution at steady state was approximately 5.8 L in patients with CAD.

Elimination

The terminal elimination half-life and clearance varies at different doses due to target-mediated drug disposition at lower sutimlimab-jome concentrations. The terminal elimination half-life (t1/2β) of sutimlimab-jome is 21 days with a clearance (CL) of approximately 0.14 L/day at the approved recommended dosage.

Metabolism

Sutimlimab-jome is a protein. It is generally recognized that antibodies are metabolized by degradation into small peptides and individual amino acids.

Specific Populations

No clinically significant differences in the pharmacokinetics of sutimlimab-jome were observed based on sex, age (19 to 88 years of age), ethnicity (Japanese, non-Japanese), and mild to moderate renal impairment (30 to 89 mL/min/1.73 m^2 measured by estimated glomerular filtration rate [eGFR]). The effects of severe renal impairment and hepatic impairment on the pharmacokinetics of sutimlimab-jome are unknown.

Body weight

Population pharmacokinetic analysis shows that sutimlimab-jome AUC at steady-state decreased up to 40% for a patient weighing 110 kg following the 7.5 g dose and increased up to 170% for a patient weighing 40 kg following the 6.5 g dose as compared with a patient weighing 70 kg following the 6.5 g dose. The effect of body weight on pharmacokinetics has been integrated in the recommended dose regimen tiered by body weight.

12.6 Immunogenicity

The observed incidence of anti-drug antibodies is highly dependent on the sensitivity and specificity of the assay. Differences in assay methods preclude meaningful comparisons of the incidence of anti-drug antibodies in the studies described below with the incidence of anti-drug antibodies in other studies, including those of sutimlimab-jome or of other sutimlimab products.

During the treatment period in CARDINAL and CADENZA, 8/66 (12%) ENJAYMO-treated patients developed anti-sutimlimab-jome antibodies (duration of exposure up to 177 weeks). There was no identified clinically significant effect of anti-drug antibodies on pharmacokinetics, pharmacodynamics, safety, or effectiveness of ENJAYMO over the treatment duration [see Clinical Studies (14)].

13 NONCLINICAL TOXICOLOGY

13.1 Carcinogenesis, Mutagenesis, Impairment of Fertility

Carcinogenicity and mutagenicity studies have not been conducted with sutimlimab-jome.

Effects of sutimlimab-jome on male and female fertility have not been studied in animals. In repeat-dose studies in cynomolgus monkeys with sutimlimab-jome administered once-weekly at exposures 3 to 4 times the human exposures at the maximum recommended human doses of sutimlimab-jome, no effects on male or female reproductive tissues were observed.

14 CLINICAL STUDIES

14.1 CADENZA

The efficacy of ENJAYMO was assessed in a placebo-controlled 6-month trial in 42 patients (CADENZA, NCT 03275454). Following the completion of the 6-month treatment period (Part A) in which 22 patients received ENJAYMO and 20 patients received placebo, 39 patients (19 patients on ENJAYMO and 20 patients on placebo) continued to receive ENJAYMO in a long-term safety and durability of response extension phase (Part B) for an additional 12 months following last patient out from Part A. The trial included a 9 week safety follow-up after the last dose of ENJAYMO. Patients with a confirmed diagnosis of CAD based on chronic hemolysis, polyspecific direct antiglobulin test (DAT), monospecific DAT specific for C3d, cold agglutinin titer ≥64 at 4°C, an IgG DAT ≤1+ and no history of transfusion within 6 months, or more than one blood transfusion in the 12 months prior to enrollment in the trial were administered 6.5 g or 7.5 g ENJAYMO (based on body weight) intravenously over approximately 60 minutes on Day 0, Day 7, and every 14 days thereafter; or placebo. Patients with cold agglutinin disease secondary to infection, rheumatologic disease, systemic lupus erythematosus, or overt hematologic malignancy were excluded, whereas patients with a history of or concomitant low-grade lymphoproliferative disease were not excluded.

Major baseline characteristics of the study population are summarized in Table 5.

Table 5: Baseline Characteristics of Patients Included in CADENZA
Parameter | Statistic | CADENZA
 |  | Placebo | ENJAYMO
 |  | N=20 | N=22
Age | Mean | 68.2 | 65.3
 | Min, Max | 51, 83 | 46, 88
Sex
Male | n (%) | 4 (20.0) | 5 (22.7)
Female |  | 16 (80.0) | 17 (77.3)
Body weight | Mean, Kg | 64.9 | 66.8
 | Min, Max | 48, 95 | 39, 100
Hemoglobin | Mean, g/dL | 9.33 | 9.15
Bilirubin (total) [Placebo N=18 and ENJAYMO N= 20 in CADENZA, for bilirubin data excluding patients with either a positive or no available test result for Gilbert's syndrome.] | µmol/L | 35.77 | 41.17
 |  | (1.75 × ULN) | (2 × ULN)
LDH | U/L | 380.8 | 421.5
History of transfusion | Mean number of transfusions (range)
Within last 6 months |  | 0 | 0
Within last 12 months |  | 0 | 0.14 (0, 1)
FACIT [ULN: Upper limit of normal, FACIT: Functional Assessment of Chronic Illness Therapy (FACIT-Fatigue is measured on a scale of 0 (worst fatigue) to 52 (no fatigue)] -Fatigue scale | Mean | 32.99 | 31.67

Efficacy was based on the proportion of patients who met the following criteria: an increase from baseline in Hgb level ≥1.5 g/dL at the treatment assessment time point (mean value from Weeks 23, 25, and 26), no blood transfusion from Week 5 through Week 26, and no treatment for CAD beyond what was permitted per protocol from Week 5 through Week 26. Efficacy was further assessed based on the effect of ENJAYMO on Hgb, laboratory measures of hemolysis including mean change from baseline in total bilirubin and LDH. Supportive efficacy data collected included transfusion usage after five weeks of treatment. In addition, mean change from baseline in symptoms and impacts of fatigue were assessed using a patient-reported outcome instrument, the FACIT-Fatigue (score range from 0 to 52 with higher scores indicating less fatigue).

The data from this study demonstrated a statistically significant treatment effect of ENJAYMO over placebo in terms of the rate of patients who met the efficacy criteria (responder) as well as improving symptoms and impacts of fatigue (FACIT-Fatigue). The responder rate difference between ENJAYMO and placebo was 58.78% (95% CI: 34.6% to 82.96%) with a p-value of 0.0004. At the treatment assessment timepoint (TAT), 16 of 22 patients on ENJAYMO (72.7%; 95% CI: 49.8% to 89.3%) and 3 of 20 patients on placebo (15.0%; 95% CI: 3.2% to 37.9%) met primary criteria. Efficacy of ENJAYMO in the inhibition of hemolysis in patients with CAD was demonstrated across multiple end points as described in the table below (see Table 6).

Table 6: Efficacy Results in Patients with CAD in the CADENZA Part A Study
Parameter | Statistic | Placebo N=20 | ENJAYMO N=22 | Treatment Effect
Responder [A responder was defined as a patient with an increase from baseline in Hgb level ≥ 1.5 g/dL at the treatment assessment time point (mean value from Weeks 23, 25, and 26), no blood transfusion from Week 5 through Week 26, and no treatment for CAD beyond what was permitted per protocol from Week 5 through Week 26.] | n (%) | 3 (15) | 16 (72.7) | 58.78 (34.6, 82.96) [The Mantel-Haenszel stratum-weighted estimator of the rate difference with 95% CI was calculated using the Sato variance estimator. The stratification factors are baseline hemoglobin (< median vs ≥ median) and geographic region (Asia/Other, North America, and Europe)]
Responder [A responder was defined as a patient with an increase from baseline in Hgb level ≥ 1.5 g/dL at the treatment assessment time point (mean value from Weeks 23, 25, and 26), no blood transfusion from Week 5 through Week 26, and no treatment for CAD beyond what was permitted per protocol from Week 5 through Week 26.] | p-value: |  |  | <0.001
Hemoglobin | Mean change from baseline (LS [LS: Least Square, FACIT-Fatigue: Functional Assessment of Chronic Illness Therapy-Fatigue Scale] Mean), g/dL | 0.09 | 2.66 | 2.56
Hemoglobin | 95% CI of LS Mean |  |  | (1.75, 3.38)
Hemoglobin | p-value: |  |  | <0.001
Patients with mean change from baseline of: greater than or equal to 1.5 g/dL | n (%) | 3 (15) | 16 (72.7) | NC
Patients not receiving blood transfusion from Week 5 through Week 26 (transfusion avoidance) | n (%) | 16 (80) | 18 (81.8) | NC
Patients not receiving protocol-prohibited CAD medications from Week 5 through Week 26 [Prohibited therapies included rituximab alone or in combination with cytotoxic agents] | n (%) | 20 (100) | 19 (86.4) | NC
FACIT-Fatigue | Mean change from baseline (LS Mean) | 1.91 | 10.83 | 8.93
FACIT-Fatigue | 95% CI of LS Mean |  |  | (4, 13.85)
FACIT-Fatigue | p-value: |  |  | <0.001
NC= Not calculated

During Part A, an increase in mean hemoglobin level of 2.02 g/dL was observed in patients on ENJAYMO at Week 3; in the placebo group the mean hemoglobin level decreased by 0.31g/dL. At treatment assessment timepoint, a mean decrease in bilirubin of 1.29 mg/dL compared to baseline was reported in patients on ENJAYMO (n=17) versus 0.11 mg/dL on placebo (n=18). In the ENJAYMO group, bilirubin levels normalized in 88.2% (n=15) of patients compared to 22.2% (n=4) of patients in the placebo arm. At treatment assessment timepoint, a mean decrease in LDH of 150.83 U/L compared to baseline was reported in patients on ENJAYMO (n=19) versus an increase of 7.6 U/L on placebo (n=20). In the ENJAYMO group, LDH levels were < 1.5 × ULN in 94.7% (n=18) of patients compared to 70% (n=14) in the placebo arm.

In Part B, mean hemoglobin levels were maintained at >10.5 g/dL. Sustained normalization of mean bilirubin levels was also observed indicating a sustained decrease in hemolysis. Mean hemoglobin level of 11.58 g/dL (range: 6.90-15.30) and 1.01 mg/dL (range: 0.29–5.54) for bilirubin was observed at the last on-treatment visit.

After the last dose of ENJAYMO in the study, signs and symptoms of recurrent hemolysis were observed, nine weeks after the last dose in Part B; mean hemoglobin decreased by 2.41 g/dL (SE: 0.373) and mean bilirubin increased by 1.27 mg/dL (SE: 0.182) from the last available values during treatment.

14.2 CARDINAL

The efficacy of ENJAYMO was assessed in an open-label, single-arm, 6-month trial in 24 patients (CARDINAL, NCT03347396). Following the completion of the 6-month treatment period (Part A), patients continued to receive ENJAYMO in a long-term safety and durability of response extension phase (Part B) for an additional 24 months following last patient out from Part A. The trial included a 9 week safety follow-up after the last dose of ENJAYMO.

Patients with a confirmed diagnosis of CAD based on chronic hemolysis, polyspecific direct antiglobulin test (DAT), monospecific DAT specific for C3d, cold agglutinin titer ≥64 at 4°C, and IgG DAT ≤1+ and a recent blood transfusion in the 6 months prior to enrollment were administered 6.5 g or 7.5 g ENJAYMO (based on body weight) intravenously over approximately 60 minutes on Day 0, Day 7, and every 14 days thereafter. Patients with cold agglutinin syndrome secondary to infection, rheumatologic disease, systemic lupus erythematosus, or overt hematologic malignancy were excluded, whereas patients with a history of or concomitant low-grade lymphoproliferative disease were not excluded. Major baseline characteristics of the trial population are summarized in Table 7.

Table 7: Baseline Characteristics of Patients Included in CARDINAL
Parameter | Statistic | ENJAYMO N=24
Age | Mean (SD) Range | 71.3 (8.2) 55 to 85 years
Sex
Female | n (%) | 15 (63)
Male |  | 9 (38)
Body weight | Mean (SD) Range | 67.8 (15.8) 40 to 112 kg
Hemoglobin | Mean (SD), g/dL | 8.6 (1.16)
Bilirubin (total) [N=21 for bilirubin data excluding patients with Gilbert's syndrome.] | Mean (SD), mg/dL | 3.1 (1.41) (2.6 × ULN [ULN: Upper limit of normal, LDH: Lactate dehydrogenase.])
LDH | Mean (SD), U/L | 438 (484.60)
Blood transfusion | Median number of transfusions (range)
Within last 6 months | Median number of transfusions (range) | 2.0 (1, 19)
Within last 12 months | Median number of transfusions (range) | 2.0 (1, 23)

Efficacy was based on the proportion of patients who met the following criteria: an increase from baseline in Hgb level ≥2 g/dL or a Hgb level ≥12 g/dL at the treatment assessment time point (mean value from Weeks 23, 25, and 26), no blood transfusion from Week 5 through Week 26, and no treatment for CAD beyond what was permitted per protocol from Week 5 through Week 26.

Efficacy of ENJAYMO in patients with CAD is described in Table 8.

Table 8: Efficacy Results in Patients with CAD in CARDINAL Part A Study
Parameter | Statistic | ENJAYMO N=24
Responder [A responder was defined as a patient with an increase from baseline in Hgb level ≥2 g/dL or a Hgb level ≥12 g/dL at the treatment assessment time point (mean value from Weeks 23, 25, and 26), no blood transfusion from Week 5 through Week 26, and no treatment for CAD beyond what was permitted per protocol from Week 5 through Week 26.] | n (%) | 13 (54)
Hemoglobin level ≥12 g/dL or Increase in Hemoglobin level of ≥2 g/dL | n (%) | 15 (63)
Hemoglobin level ≥12 g/dL | n (%) | 9 (38)
Increase in Hemoglobin level of ≥2 g/dL | n (%) | 15 (63)
Patients not receiving RBC transfusion from Week 5 through Week 26 (transfusion avoidance) | n (%) | 17 (71)
Patients not receiving protocol-prohibited CAD medications [Prohibited therapies included rituximab alone or in combination with cytotoxic agents.] from Week 5 through Week 26 | n (%) | 22 (92)

In Part A, among 14 patients with baseline and follow-up bilirubin values, the mean was 3.23 mg/dL (2.7-fold ULN) at baseline and 0.91 mg/dL (0.8-fold ULN) at the treatment assessment time point. The least-squares (LS) mean change was reduction of -2.23 mg/dL (95% CI: -2.49 to -1.98). Among 17 patients with baseline and follow-up LDH values, the mean LDH was 424 U/L (1.7-fold ULN) at baseline and 301 U/L (1.2-fold ULN) at the follow-up time point. The least squared mean change in LDH at the treatment assessment time point was reduction of -126 (95% CI: -218 to -35).

In CARDINAL, an increase in mean hemoglobin level of 2.29 g/dL (SE: 0.308) was observed at Week 3 and 3.18 g/dL (SE: 0.476) at treatment assessment time point. The observed model mean change in hemoglobin level from baseline at treatment assessment time point was an improvement of 2.60 g/dL (95% CI: 0.74, 4.46).

In Part B, mean hemoglobin levels were maintained at >10 g/dL. Sustained normalization of mean bilirubin levels was also observed indicating a sustained decrease in hemolysis. Mean hemoglobin level of 12.23 g/dL (range: 9.20–14.40) and 0.96 mg/dL (range: 0.4–1.7) for bilirubin was observed at the last on-treatment visit.

After the last dose of ENJAYMO in the study, signs and symptoms of recurrent hemolysis were observed, nine weeks after the last dose in Part B; mean hemoglobin decreased by 2.28 g/dL (SE: 0.402) and mean bilirubin increased by 1.42 mg/dL (SE: 0.192) from the last available values during treatment.

16 HOW SUPPLIED/STORAGE AND HANDLING

How Supplied

ENJAYMO (sutimlimab-jome) injection is a clear to slightly opalescent, colorless to slightly yellow, preservative-free solution supplied as one 1,100 mg/22 mL (50 mg/mL) single-dose vial per carton (NDC 55292-820-01).

Storage and Handling

Store ENJAYMO vials refrigerated at 36°F to 46°F (2°C to 8°C) in the original carton to protect from light. Do not freeze. Do not shake.

Discard unused portion.

17 PATIENT COUNSELING INFORMATION

Advise the patient to read the FDA-approved patient labeling (Medication Guide).

Serious Infections Including Those Caused by Encapsulated Bacteria

Advise patients of the risk of serious infection. Inform patients of the need to complete or update their vaccinations against encapsulated bacteria at least 2 weeks prior to receiving the first dose of ENJAYMO. If urgent ENJAYMO therapy is indicated in a patient who is not up to date on their vaccines administer vaccine(s) as soon as possible. Inform the patient that they are required to be revaccinated according to current ACIP recommendations for encapsulated bacteria while on ENJAYMO therapy [see Warnings and Precautions (5.1)].

Inform patients that vaccination may not prevent serious infection and strongly advise the patient to seek immediate medical attention if signs or symptoms of serious infection occur. These signs and symptoms include the following:

- fever with or without shivers or the chills
- fever and a rash
- fever with chest pain and cough
- fever with breathlessness/fast breathing
- fever with high heart rate
- headache with nausea or vomiting
- headache and a fever
- headache with a stiff neck or stiff back
- confusion
- body aches with flu-like symptoms
- clammy skin
- eyes sensitive to light

Infusion-Related Reactions

Advise patients that administration of ENJAYMO may result in infusion-related reactions including hypersensitivity reactions. Hypersensitivity reactions may be serious or life-threatening (e.g., anaphylaxis). Educate patients on the symptoms of infusion-related reactions and advise them to seek medical attention if any new symptoms of infusion-related reactions occur [see Contraindications (4) and Warnings and Precautions (5.2)].

Risk of Autoimmune Disease

Educate patients that there may be an increased risk of developing an autoimmune disease such as SLE during ENJAYMO therapy. Advise patients on signs and symptoms of SLE and to report any new symptoms of SLE and seek medical attention [see Warnings and Precautions (5.3)].

Discontinuation

Inform patients with CAD that they may develop hemolysis due to CAD when ENJAYMO is discontinued and that they should be monitored by their healthcare provider following ENJAYMO discontinuation [see Warnings and Precautions (5.4)].

This product's labeling may have been updated. For the most recent prescribing information, please visit www.enjaymo.com.

Manufactured by:
Recordati Rare Diseases Inc.
Bridgewater, NJ 08807

US License No. 1899

©2024 Recordati Rare Diseases Inc. All rights reserved.

MEDICATION GUIDE
ENJAYMO® (en-jaye-moe)
(sutimlimab-jome)
injection, for intravenous use

What is the most important information I should know about ENJAYMO?
ENJAYMO is a medicine that affects your immune system. ENJAYMO may lower the ability of your immune system to fight infections.

- ENJAYMO increases your chance of getting serious infections including those caused by encapsulated bacteria, including Neisseria meningitidis, Streptococcus pneumoniae, and Haemophilus influenzae type B. These serious infections may quickly become life-threatening or cause death if not recognized and treated early.
  - You must complete or be up to date with the vaccines against Streptococcus pneumoniae and Neisseria meningitidis at least 2 weeks before your first dose of ENJAYMO.
  - If your healthcare provider decides that urgent treatment with ENJAYMO is needed, you should receive vaccinations as soon as possible.
  - If you have been vaccinated against these bacteria in the past, you might need additional vaccines before starting ENJAYMO. Your healthcare provider will decide if you need additional vaccines.
  - Vaccines do not prevent all infections caused by encapsulated bacteria. Call your healthcare provider or get emergency medical care right away if you get any of these signs and symptoms of a serious infection:

- fever with or without shivers or chills
- fever with chest pain and cough
- fever with high heart rate
- headache and fever
- confusion
- clammy skin

- fever and a rash
- fever with breathlessness or fast breathing
- headache with nausea or vomiting
- headache with stiff neck or stiff back
- body aches with flu-like symptoms
- eyes sensitive to light

For more information about side effects, see "What are the possible side effects of ENJAYMO?"

What is ENJAYMO?

ENJAYMO is a prescription medicine used to treat the breakdown of red blood cells (hemolysis) in adults with cold agglutinin disease (CAD).
It is not known if ENJAYMO is safe and effective in children.

Who should not receive ENJAYMO?

Do not receive ENJAYMO if you are allergic to sutimlimab-jome or any of the ingredients in ENJAYMO. See the end of this Medication Guide for a complete list of ingredients in ENJAYMO.

Before receiving ENJAYMO, tell your healthcare provider about all of your medical conditions, including if you:

- have a fever or infection, including a history of human immunodeficiency virus (HIV), hepatitis B, or hepatitis C.
- have an autoimmune disease such as systemic lupus erythematosus (SLE), also known as lupus.
- are pregnant or plan to become pregnant. It is not known if ENJAYMO will harm your unborn baby.
- are breastfeeding or plan to breastfeed. It is not known if ENJAYMO passes into your breast milk. You should talk to your healthcare provider about the best way to feed your baby during treatment with ENJAYMO.

Tell your healthcare provider about all the medicines you take, including prescription and over-the-counter medicines, vitamins, and herbal supplements.
Know the medicines you take. Keep a list of them to show your healthcare provider and pharmacist when you get a new medicine.

How will I receive ENJAYMO?

- ENJAYMO is given through a vein by intravenous (I.V.) infusion, usually over 1 to 2 hours.
- You will usually receive a starting dose of ENJAYMO, followed by a second dose of ENJAYMO 1 week later. Then 2 weeks after your second dose, you will start to receive an ENJAYMO infusion every 2 weeks.
- After your first infusion, you should be monitored for infusion and allergic reactions for at least 2 hours. For all future infusions, you should be monitored for infusion reactions for 1 hour. See "What are the possible side effects of ENJAYMO?"
- If you have CAD and you stop receiving ENJAYMO, your healthcare provider should monitor you closely for return of your symptoms after you stop ENJAYMO. Stopping ENJAYMO may cause the breakdown of your red blood cells due to CAD to return. Symptoms or problems that can happen due to red blood cell breakdown include:

- tiredness
- shortness of breath

- rapid heart rate
- blood in your urine or dark urine

- If you miss an ENJAYMO infusion, call your healthcare provider right away.

What are the possible side effects of ENJAYMO?
ENJAYMO can cause serious side effects, including:

- See "What is the most important information I should know about ENJAYMO?"
- Infusion-related reactions. Treatment with ENJAYMO may cause infusion-related reactions, including allergic reactions that may be serious or life-threatening. Your healthcare provider may slow down or stop your ENJAYMO infusion if you have an infusion-related reaction and will treat your symptoms if needed. Tell your healthcare provider right away if you develop symptoms during your ENJAYMO infusion that may mean you are having an infusion-related reaction, including:

- shortness of breath
- decrease in blood pressure
- chest discomfort
- rapid heartbeat
- nausea
- injection site reaction

- flushing
- headache
- dizziness
- rash
- itchy skin

- Risk of autoimmune disease. ENJAYMO may increase your risk for developing an autoimmune disease such as SLE. Tell your healthcare provider and get medical help if you develop any symptoms of SLE, including:
  - joint pain or swelling
  - rash on the cheeks and nose
  - unexplained fever

The most common side effects of ENJAYMO include:

- increase in blood pressure
- urinary tract infection
- respiratory tract infection
- bacterial infection
- swelling in lower legs or hands
- joint pain
- headache

- nausea
- runny nose
- bluish color to the lips and skin
- dizziness
- feeling tired or weak
- cough
- changes in color or sensation in the fingers and toes (Raynaud's phenomenon)

These are not all the possible side effects of ENJAYMO.
Call your doctor for medical advice about side effects. You may report side effects to FDA at 1-800-FDA-1088.

General information about the safe and effective use of ENJAYMO.

Medicines are sometimes prescribed for purposes other than those listed in a Medication Guide. You can ask your pharmacist or healthcare provider for information about ENJAYMO that is written for health professionals.

What are the ingredients in ENJAYMO?

Active ingredient: sutimlimab-jome

Inactive ingredients: polysorbate 80, sodium chloride, sodium phosphate dibasic heptahydrate, sodium phosphate monobasic monohydrate, and Water for Injection, USP.

Manufactured by: Recordati Rare Diseases Inc., Bridgewater, NJ 08807
US License No. 1899
For more information, go to www.ENJAYMO.com or call 1-888-575-8344.
©2024 Recordati Rare Diseases Inc. All rights reserved.

This Medication Guide has been approved by the U.S. Food and Drug Administration.

Revised:11/2024

PRINCIPAL DISPLAY PANEL - 1,100 mg/22 mL Vial Carton

NDC 55292-820-01
Rx only

Enjaymo®
(sutimlimab-jome)
Injection

1,100 mg/22 mL (50 mg/mL)

For Intravenous Infusion

Attention Pharmacist:
Each patient is required to receive the
enclosed Medication Guide

One single-dose vial
Discard unused portion

RECORDATI
RARE DISEASES